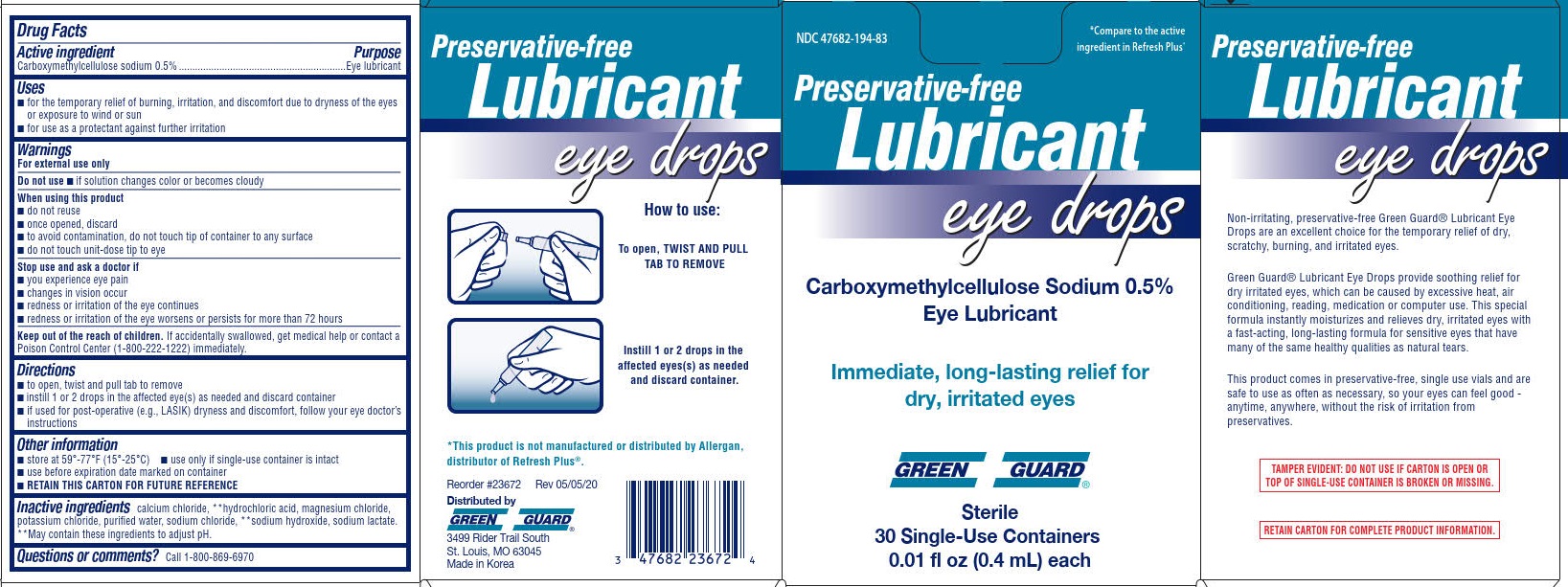 DRUG LABEL: Green Guard Lubricant Eye Drops
NDC: 47682-194 | Form: SOLUTION
Manufacturer: UniFirst First Aid Corporation
Category: otc | Type: HUMAN OTC DRUG LABEL
Date: 20251230

ACTIVE INGREDIENTS: CARBOXYMETHYLCELLULOSE SODIUM, UNSPECIFIED 0.5 g/100 mL
INACTIVE INGREDIENTS: MAGNESIUM CHLORIDE; POTASSIUM CHLORIDE; WATER; SODIUM HYDROXIDE; SODIUM LACTATE; SODIUM CHLORIDE; HYDROCHLORIC ACID; CALCIUM CHLORIDE

Green Guard Lubricant Eye Drops (PLD)

Drug Facts

Active ingredient

Carboxymethylcellulose sodium 0.5%

Purpose

Eye lubricant

Uses

- for the temporary relief of burning, irritation, and discomfort due to dryness of the eyes or exposure to wind or sun
- for use a protectant against further irritation

Warnings

For external use only

Do not use

- if solution changes color or becomes cloudy

When using this product

- do not reuse
- once opened, discard
- to avoid contamination, do not touch tip of container to any surface
- do not touch unit-dose tip to eye

Stop use and ask a doctor if

- you experience eye pain
- changes in vision occur
- redness or irritation of the eye continues
- redness or irritation of the eye worsens or persists for more than 72 hours

Keep out od reach of children.

If accidentally swallowed, get medical help or contact a Poison Control Center (1-800-222-1222) immediately.

Directions

- to open, twist and pull tab to remove
- instill 1 or 2 drops in the affected eye(s) as needed and discard container
- if used for post-operative (e.g.,LASIK) dryness and discomfort, follow your eye doctor's instructions

Other information

- store at 59º-77ºF (15º-25ºC)
- use only if single-use container is intact
- use before expiration date marked on container
- RETAIN THIS CARTON FOR FUTURE REFERENCE

Inactive ingredients

calcium chloride, **hydrochloric acid, magmesium chloride, potassium chloride, purified water, sodium chloride, **sodium hydroxide, sodium lactate

** May contain these ingredients to adjust pH

Questions or comments?1-800-869-6970

PACKAGE LABEL

Preservative-free

Lubricant eye drops

NDC 47682-194-84

*Compare to the active ingredients in Refresh Plus®

Carboxymethylcellulose Sodium 0.5% Eye Lubricant

Immediate, long-lasting relief for dry, irritated eyes

Green Guard

Sterile

30 Single-Use Containers

0.01 fl oz (0.4 mL) each